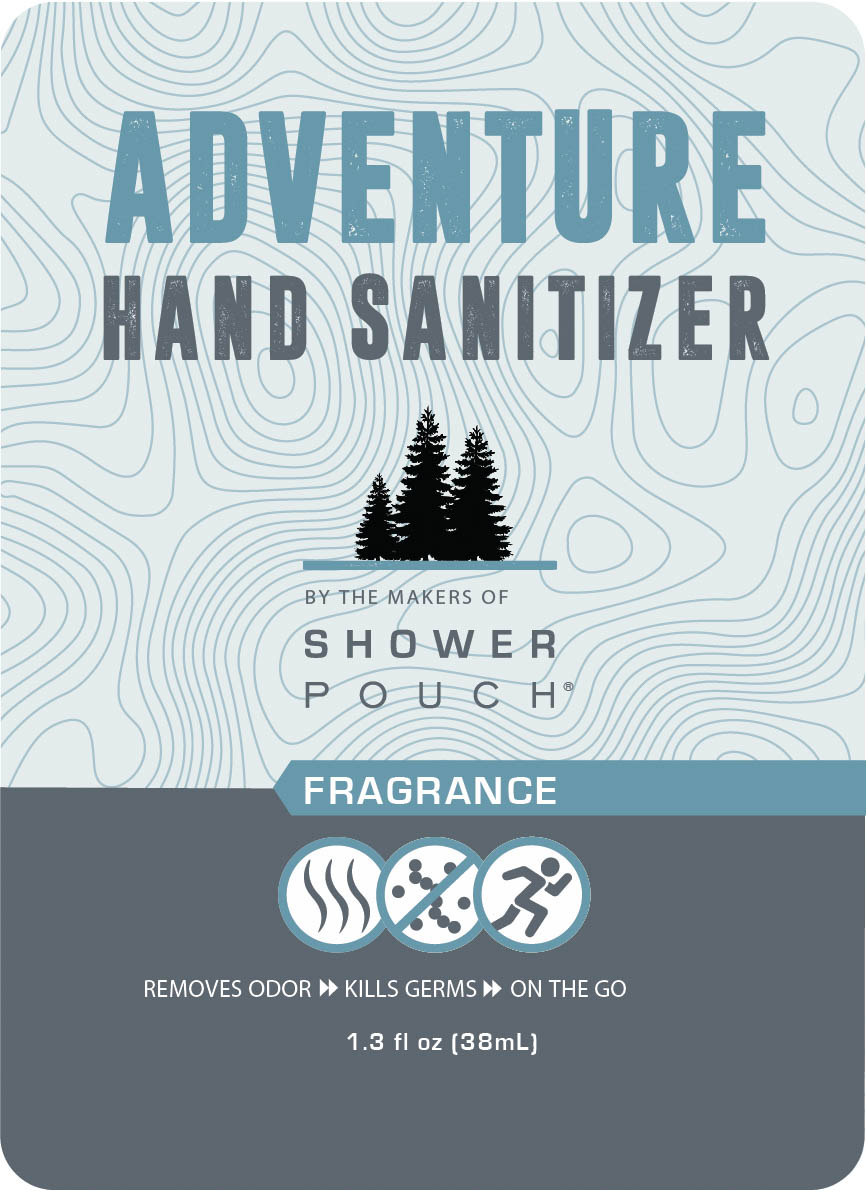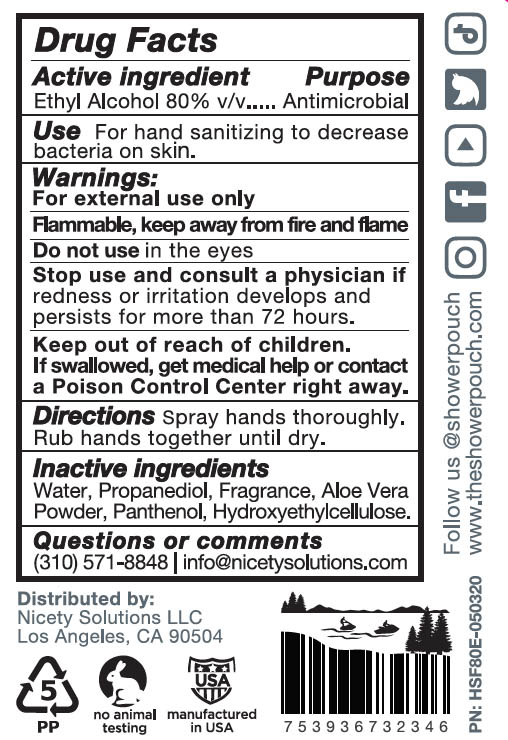 DRUG LABEL: Adventure Hand Sanitizer - Fragrance 80%
NDC: 77371-124 | Form: SPRAY
Manufacturer: NICETY SOLUTIONS LLC
Category: otc | Type: HUMAN OTC DRUG LABEL
Date: 20260129

ACTIVE INGREDIENTS: ALCOHOL 0.8 mL/1 mL
INACTIVE INGREDIENTS: WATER; ALOE VERA LEAF; PANTHENOL; HYDROXYETHYL CELLULOSE, UNSPECIFIED; PROPANEDIOL

Adventure Hand Sanitizer 80% Ethyl Alcohol Fragrance

Active ingredient

Ethyl Alcohol 80% v/v

Purpose

Antimicrobial

Use

For hand sanitizing to decrease bacteria on skin.

Warnings

For external use only

Flammable, keep away from fire and flame

Do not use

in the eyes

Keep out of reach of children

If swallowed, get medical help or contact an Poison Control Center right away.

Stop use and ask a doctor if

redness or irritation develops and persists for more than 72 hours

Directions

Spray hands thoroughly. Rub hands together until dry.

Inactive ingredients

Water, Propanediol, Aloe Vera Powder, Panthenol, Hydroxyethylcellulose

Label

Adventure Hand Santitizer

By the makers of Shower Pouch

Remove odors

Kills germs on the go

1.3 fl oz [38 ml]